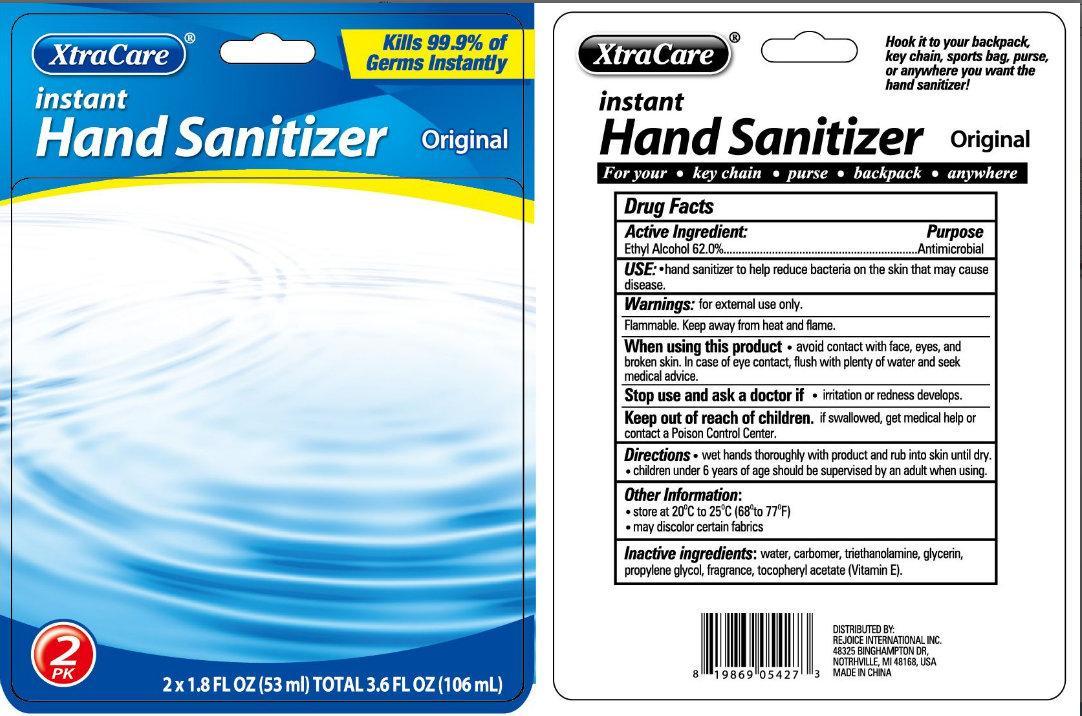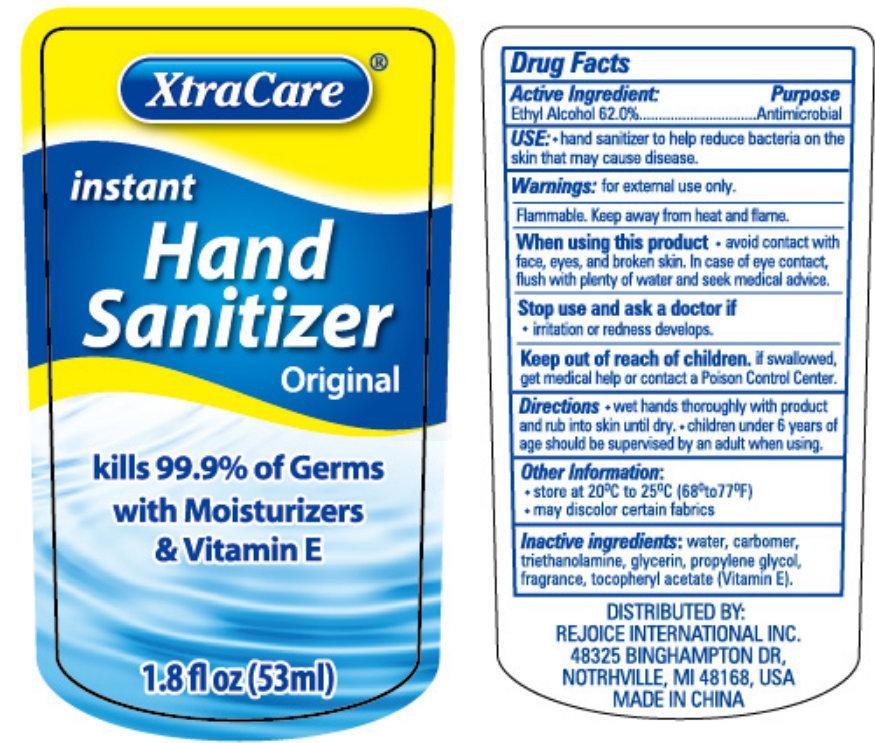 DRUG LABEL: XtraCare instant Hand Sanitizer Original
NDC: 57337-000 | Form: LIQUID
Manufacturer: Rejoice International
Category: otc | Type: HUMAN OTC DRUG LABEL
Date: 20130228

ACTIVE INGREDIENTS: ALCOHOL 62 mL/100 mL
INACTIVE INGREDIENTS: WATER; TROLAMINE; GLYCERIN; PROPYLENE GLYCOL; .ALPHA.-TOCOPHEROL ACETATE

XtraCare instant Hand Sanitizer Original

Active ingredient:

Ethyl Alcohol 62.0%

Purpose

Antimicrobial

USE:

- hand sanitizer to help reduce bacteria on the skin that may cause disease.

Warnings:

for external use only.
Flammable. Keep away from heat and flame.

When using this product

- avoid contact with face, eyes, and broken skin. In case of eye contact, flush with plenty of water and seek medical advice.

Stop use and ask a doctor if

- irritation or redness develops.

Keep out of reach of children.

if swallowed, get medical help or contact a Poison Control Center.

Directions

- wet hands thoroughly with product and rub into skin until dry.
- children under 6 years of age should be supervised by an adult when using.

Other Information:

- store at 20^0C to 25^0C (68^0 to 77^0F)
- may discolor certain fabrics.

Inactive ingredients:

water, carbomer, triethanolamine, glycerin, propylene glycol, fragrance, tocopheryl acetate (Vitamin E).

XtraCare

Hook it to your backpack, key chain, sports bag, purse, or anywhere you want the hand sanitizer!
DISTRIBUTED BY: REJOICE INTERNATIONAL INC. 48325 BINGHAMPTON DR, NOTRHVILLE, MI 48168, USA
MADE IN CHINA.

PACKAGE LABEL

XtraCare instant Hand Sanitizer Original Kills 99.9% of Germs Instantly 2PK 2 X 1.8 FL OZ (53 ml) TOTAL 3.6 FL OZ (106 mL)